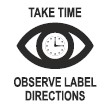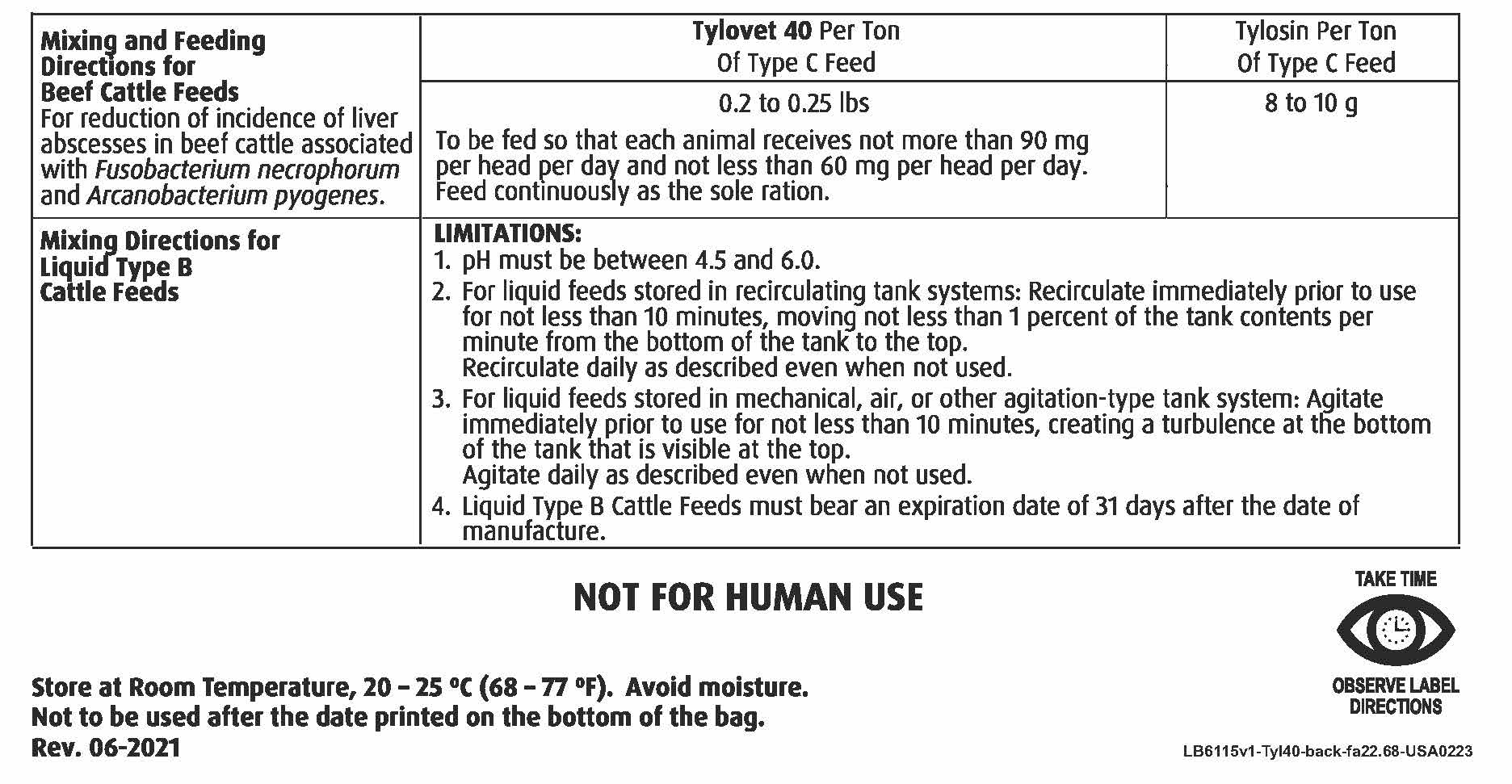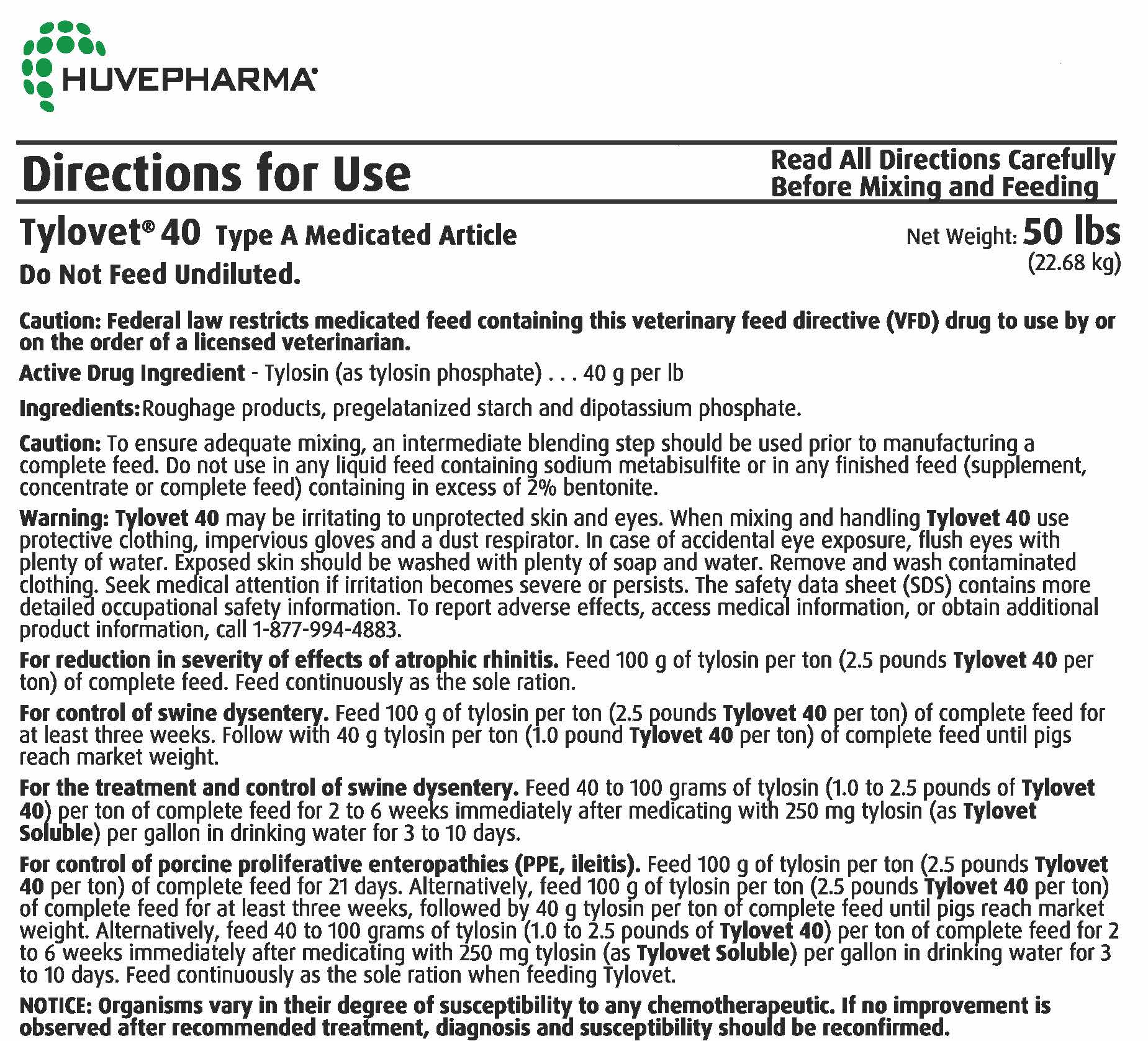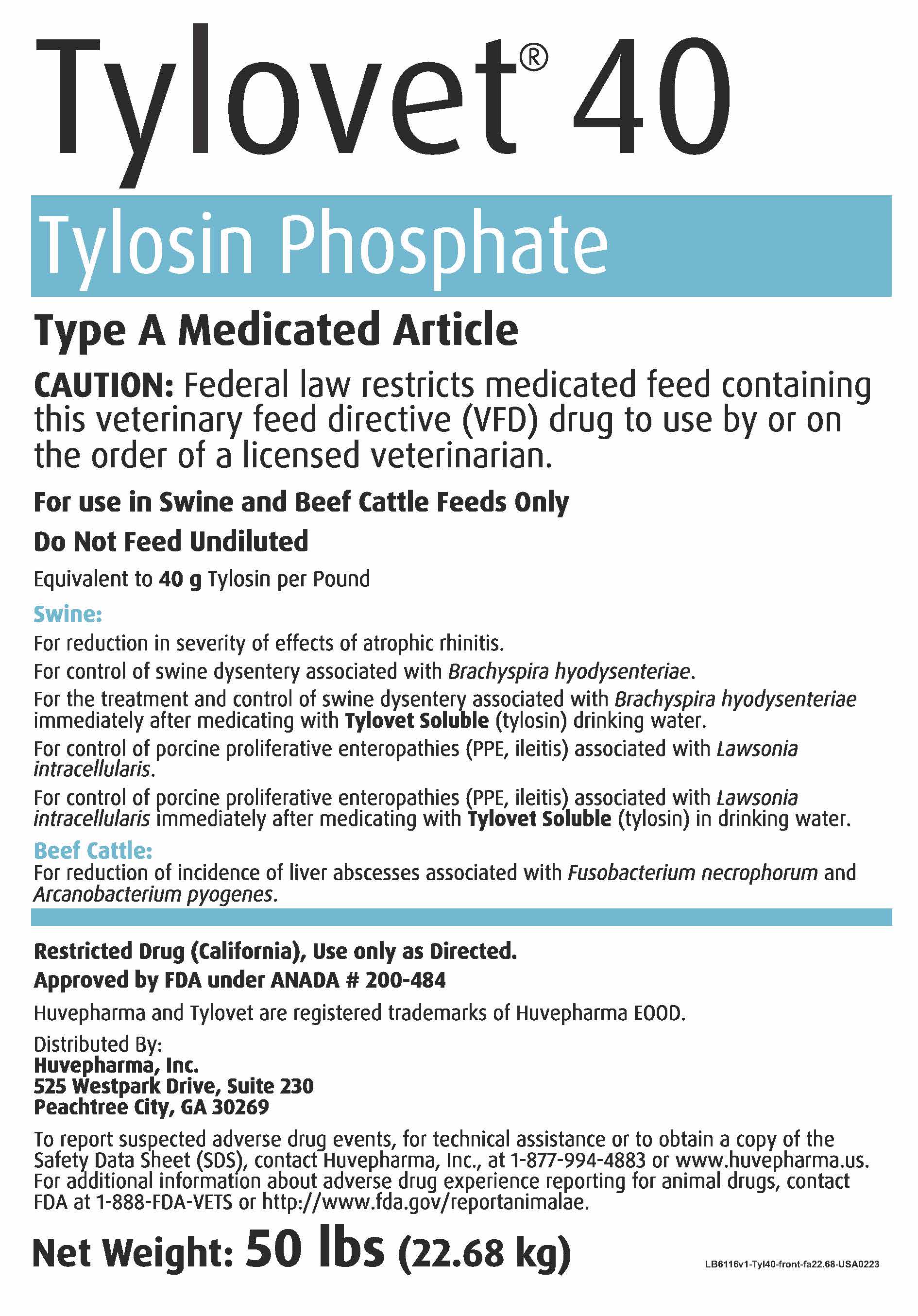 DRUG LABEL: Tylovet 40
NDC: 23243-2355 | Form: POWDER
Manufacturer: Huvepharma, Inc.
Category: animal | Type: VFD TYPE A MEDICATED ARTICLE ANIMAL DRUG LABEL
Date: 20230411

ACTIVE INGREDIENTS: TYLOSIN PHOSPHATE 40 g/0.45 kg

Tylovet® 40
Tylosin Phosphate
Type A Medicated Article

PRECAUTIONS

CAUTION: Federal law restricts medicated feed containing this veterinary feed directive (VFD) drug to use by or on

the order of a licensed veterinarian.

For use in Swine and Beef Cattle Feeds Only

Do Not Feed Undiluted

INDICATIONS AND USAGE

Equivalent to 40 g Tylosin per Pound

Swine:
For the reduction in severity of effects of atrophic rhinitis.

For control of swine dysentery associated with Brachyspira hyodysenteriae.

For the treatment and control of swine dysentery associated with Brachyspira
hyodysenteriae immediately after medicating with Tylovet Soluble (tylosin)
drinking water.

For control of porcine proliferative enteropathies (PPE, ileitis) associated with
Lawsonia intracellularis.

For control of porcine proliferative enteropathies (PPE, ileitis) associated with
Lawsonia intracellularis immediately after medicating with Tylovet Soluble (tylosin)
in drinking water.

Beef Cattle:
For reduction of incidence of liver abscesses associated with Fusobacterium
necrophorum and Arcanobacterium pyogenes.

GENERAL PRECAUTIONS

Restricted Drug (California) Use Only as Directed.
Approved by FDA under ANADA # 200-484
Huvepharma and Tylovet are registered trademarks of Huvepharma EOOD.

Distributed By:
Huvepharma, Inc.
525 Westpark Drive, Suite 230
Peachtree City, GA 30269

ADVERSE REACTIONS

To report suspected adverse drug events, for technical assistance or to obtain
a copy of the Safety Data Sheet (SDS), contact Huvepharma, Inc., at
1-877-994-4883 or www.huvepharma.us. For additional information about adverse
drug experience reporting for animal drugs, contact FDA at 1-888-FDA-VETS or
http://www.fda.gov/reportanimalae.

Net Weight: 50 lbs (22.68 kg)

INDICATIONS AND USAGE

Directions for Use Read All Directions Carefully
Before Mixing and Feeding

Tylovet® 40 Type A Medicated Article Net Weight: 50 lbs

Do Not Feed Undiluted. (22.68 kgs)

CAUTION: Federal law restricts medicated feed containing this veterinary feed directive (VFD)
drug to use by or on the order of a licensed veterinarian.

Active Drug Ingredient: Tylosin (as tylosin phosphate)...40 g per lb

Ingredients: Roughage products, pregelatanized starch and dipotassium phosphate.

Caution: To ensure adequate mixing, an intermediate blending step should be used prior to
manufacturing a complete feed. Do not use in any liquid feed containing sodium metabisulfite
or in any finished feed (supplement, concentrate or complete feed) containing in excess of 2%
bentonite.

Warning: Tylovet 40 may be irritating to unprotected skin and eyes. When mixing and handling
Tylovet 40 use protective clothing, impervious gloves and a dust respirator. In case of
accidental eye exposure, flush eyes with plenty of water. Exposed skin should be washed with plenty
of soap and water. Remove and wash contaminated clothing. Seek medical attention if irritation
becomes severe or persists. The Safety Data Sheet (SDS) contains more detailed occupational
safety information. To report adverse effects, access medical information, or obtain additional
product information, call 1-877-994-4883.

For reduction in severity of effects of atrophic rhinitis. Feed 100 g of tylosin per ton
(2.5 pounds Tylovet 40 per ton) of complete feed. Feed continuously as the sole ration.

For control of swine dysentery. Feed 100 g of tylosin per ton (2.5 pounds Tylovet 40 per ton)
of complete feed for at least three weeks. Follow with 40 g tylosin per ton (1.0 pound
Tylovet 40 per ton) of complete feed until pigs reach market weight.

For the treatment and control of swine dysentery. Feed 40 to 100 grams of tylosin (1.0 to
2.5 pounds of Tylovet 40) per ton of complete feed for 2 to 6 weeks immediately after
medicating with 250 mg tylosin (as Tylovet Soluble) per gallon in drinking water for 3 to 10
days.

For the control of porcine proliferative enteropathies (PPE, ileitis). Feed 100 g tylosin
per ton (2.5 pound Tylovet 40 per ton) of complete feed for 21 days. Alternatively, feed 100 g
of tylosin per ton (2.5 pound Tylovet 40 per ton) of complete feed for at least three weeks,
followed by 40 g tylosin per ton of complete feed until pigs reach market weight. Alternatively,
feed 40 to 100 grams of tylosin (1.0 to 2.5 pounds of Tylovet 40) per ton of complete feed for 2
to 6 weeks immediately after medicating with 250 mg tylosin (as Tylovet Soluble) per gallon in
drinking water for 3 to 10 days. Feed continuously as the sole ration when feeding Tylovet.

NOTICE: Organisms vary in their degree of susceptibility to any chemotherapeutic. If no
improvement is observed after recommended treatment, diagnosis and susceptibility should be
reconfirmed.

Mixing and Feeding Directions for Beef Cattle Feeds For reduction of incidence of liver abscesses in beef cattle associated with Fusobacterium necrophorum and Arcanobacterium pyogenes | Tylovet 40 per Ton Of Type C Feed | Tylosin Per Ton of Type C Feed
Mixing and Feeding Directions for Beef Cattle Feeds For reduction of incidence of liver abscesses in beef cattle associated with Fusobacterium necrophorum and Arcanobacterium pyogenes | 0.2 to 0.25 lbs; To be fed so that each animal receives not more than 90 mg per head per day and not less than 60 mg per head per day. Feed continuously as the sole ration. | 8 to 10 g
Mixing Directions for Liquid Type B Cattle Feeds | LIMITATIONS: 1. pH must be between 4.5 and 6.0. 2. For liquid feeds stored in recirculating tank systems: Recirculate immediately prior to use for not less than 10 minutes, moving not less than 1 percent of the tank contents per minute from the bottom of the tank to the top. Recirculate daily as described even when not used. 3. For liquid feeds stored in mechanical, air, or other agitation-type tank systems: Agitate immediately prior to use for not less than 10 minutes, creating a turbulence at the bottom of the tank that is visible at the top. Agitate daily as described even when not used. 4. Liquid Type B Cattle Feeds must bear an expiration date of 31 days after the date of manufacture.

NOT FOR HUMAN USE

STORAGE AND HANDLING

Store at Room Temperature, 20 - 25°C (68 - 77°F). Avoid moisture.
Not to be used after the date printed on the bottom of the bag.
Rev. 06-2021